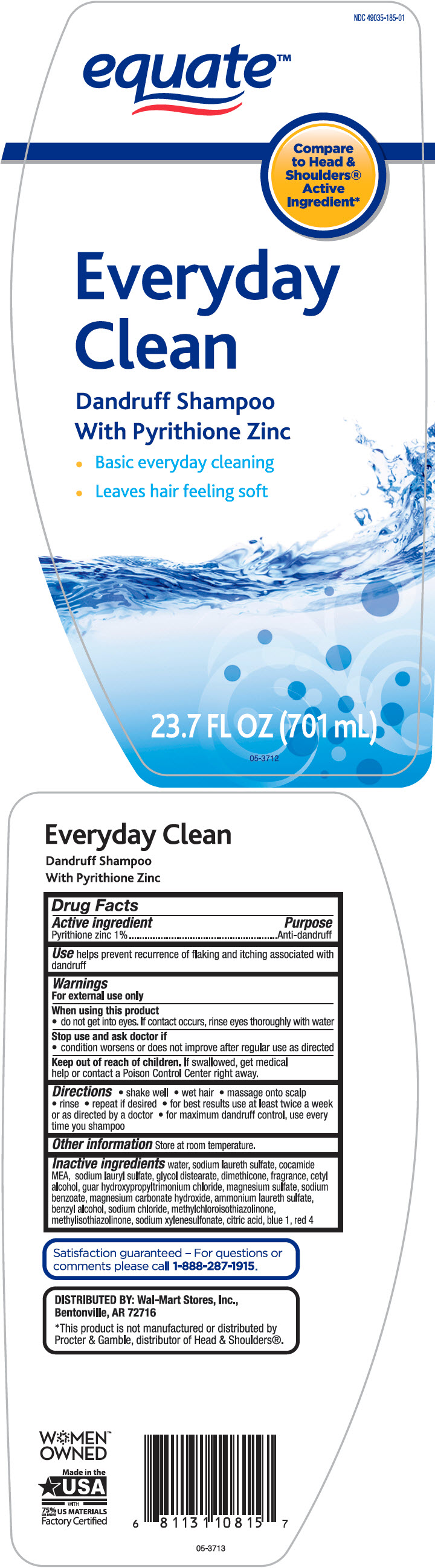 DRUG LABEL: Equate Everyday Clean Dandruff
NDC: 49035-185 | Form: SHAMPOO
Manufacturer: Wal-Mart Stores, Inc.
Category: otc | Type: HUMAN OTC DRUG LABEL
Date: 20231214

ACTIVE INGREDIENTS: Pyrithione Zinc 10 mg/1 mL
INACTIVE INGREDIENTS: Water; Sodium Laureth-3 Sulfate; Coco Monoethanolamide; Sodium Lauryl Sulfate; Glycol Distearate; Dimethicone; Cetyl Alcohol; Guar Hydroxypropyltrimonium Chloride (1.7 Substituents Per Saccharide); Magnesium Sulfate, Unspecified Form; Sodium Benzoate; Magnesium Carbonate Hydroxide; Ammonium Laureth-5 Sulfate; Benzyl Alcohol; Sodium Chloride; Methylchloroisothiazolinone; Methylisothiazolinone; Sodium Xylenesulfonate; Citric Acid Monohydrate; FD&C Blue No. 1; FD&C Red No. 4

Equate™ Everyday Clean Dandruff Shampoo
Anti-Dandruff

Drug Facts

Active ingredient

Pyrithione Zinc 1%

Purpose

Anti-dandruff

Use

helps prevent recurrence of flaking and itching associated with dandruff

Warnings

For external use only

When using this product

- do not get into eyes. If contact occurs, rinse eyes thoroughly with water

Stop use and ask a doctor if

- condition worsens or does not improve after regular use as directed

Keep out of reach of children. If swallowed, get medical help or contact a Poison Control Center right away

Directions

- shake well
- wet hair
- massage onto scalp
- rinse
- repeat if desired
- for best results use at least twice a week or as directed by a doctor
- for maximum dandruff control, use every time you shampoo

Other information

store at room temperature

Inactive ingredients

water, sodium laureth sulfate, cocamide MEA, sodium lauryl sulfate, glycol distearate, dimethicone, fragrance, cetyl alcohol, guar hydroxypropyltrimonium chloride, magnesium sulfate, sodium benzoate, magnesium carbonate hydroxide, ammonium laureth sulfate, benzyl alcohol, sodium chloride, methylchloroisothiazolinone, methylisothiazolinone, sodium xylenesulfonate, citric acid, blue 1, red 4

QUESTIONS

Satisfaction guaranteed – For questions or comments please call 1-888-287-1915.

DISTRIBUTED BY: Wal-Mart Stores, Inc.,
Bentonville, AR 72716

PRINCIPAL DISPLAY PANEL - 701 mL Bottle Label

NDC 49035-185-01

equate™

Compare
to Head &
Shoulders®
Active
Ingredient*

Everyday
Clean

Dandruff Shampoo
With Pyrithione Zinc

- Basic everyday cleaning
- Leaves hair feeling soft

23.7 FL OZ (701 mL)

05-3712